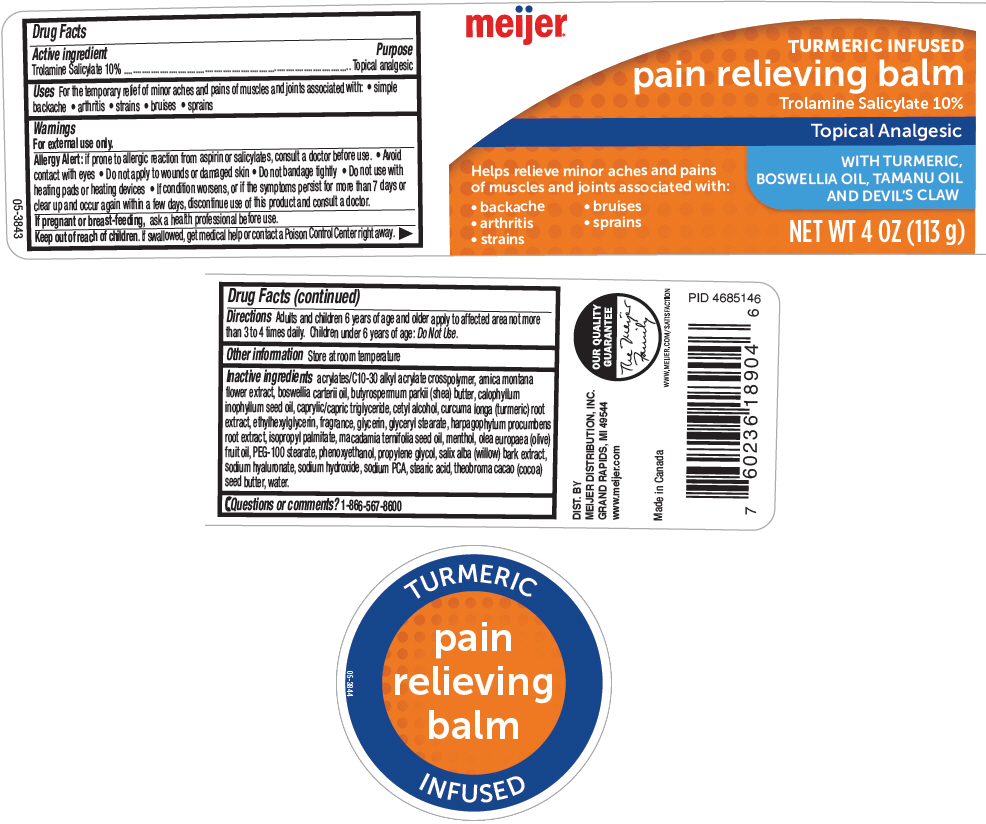 DRUG LABEL: Meijer Pain Relieving Balm
NDC: 41250-356 | Form: CREAM
Manufacturer: Meijer Distribution, Inc
Category: otc | Type: HUMAN OTC DRUG LABEL
Date: 20241107

ACTIVE INGREDIENTS: Trolamine Salicylate 10 mg/1 g
INACTIVE INGREDIENTS: CARBOMER INTERPOLYMER TYPE A (ALLYL SUCROSE CROSSLINKED); ARNICA MONTANA FLOWER; FRANKINCENSE OIL; SHEA BUTTER; TAMANU OIL; MEDIUM-CHAIN TRIGLYCERIDES; Cetyl Alcohol; TURMERIC; Ethylhexylglycerin; Glycerin; GLYCERYL MONOSTEARATE; HARPAGOPHYTUM PROCUMBENS ROOT; Isopropyl Palmitate; MACADAMIA OIL; MENTHOL, UNSPECIFIED FORM; OLIVE OIL; PEG-100 Stearate; Phenoxyethanol; Propylene Glycol; SALIX ALBA BARK; HYALURONATE SODIUM; Sodium Hydroxide; SODIUM PYRROLIDONE CARBOXYLATE; Stearic Acid; COCOA BUTTER; Water

Meijer® Pain Relieving Balm
Topical Analgesic

Drug Facts

Active ingredient

Trolamine Salicylate 10%

Purpose

Topical analgesic

Uses

For the temporary relief of minor aches and pains of muscles and joints associated with:

- simple backache
- arthritis
- strains
- bruises
- sprains

Warnings

For external use only.

Allergy Alert: if prone to allergic reaction from aspirin or salicylates, consult a doctor before use.

- Avoid contact with eyes
- Do not apply to wounds or damaged skin
- Do not bandage tightly
- Do not use with heating pads or heating devices
- If condition worsens, or if the symptoms persist for more than 7 days or clear up and occur again within a few days, discontinue use of this product and consult a doctor.

PREGNANCY OR BREAST FEEDING

If pregnant or breast-feeding, ask a health professional before use.

Keep out of reach of children. If swallowed, get medical help or contact a Poison Control Center right away.

Directions

Adults and children 6 years of age and older apply to affected area not more than 3 to 4 times daily. Children under 6 years of age: Do Not Use.

Other information

Store at room temperature

Inactive ingredients

acrylates/C10-30 alkyl acrylate crosspolymer, arnica montana flower extract, boswellia carterii oil, butyrospermum parkii (shea) butter, calophyllum inophyllum seed oil, caprylic/capric triglyceride, cetyl alcohol, curcuma longa (turmeric) root extract, ethylhexylglycerin, fragrance, glycerin, glyceryl stearate, harpagophytum procumbens root extract, isopropyl palmitate, macadamia ternifolia seed oil, menthol, olea europaea (olive) fruit oil, PEG-100 stearate, phenoxyethanol, propylene glycol, salix alba (willow) bark extract, sodium hyaluronate, sodium hydroxide, sodium PCA, stearic acid, theobroma cacao (cocoa) seed butter, water.

Questions or comments?

1-866-567-8600

DIST. BY
MEIJER DISTRIBUTION, INC.
GRAND RAPIDS, MI 49544

PRINCIPAL DISPLAY PANEL - 113 g Jar Label

meijer®

TURMERIC INFUSED
pain relieving balm
Trolamine Salicylate 10%

Topical Analgesic

WITH TURMERIC,
BOSWELLIA OIL, TAMANU OIL
AND DEVIL'S CLAW

Helps relieve minor aches and pains
of muscles and joints associated with:

- backache
- bruises
- arthritis
- sprains
- strains

NET WT 4 OZ (113 g)